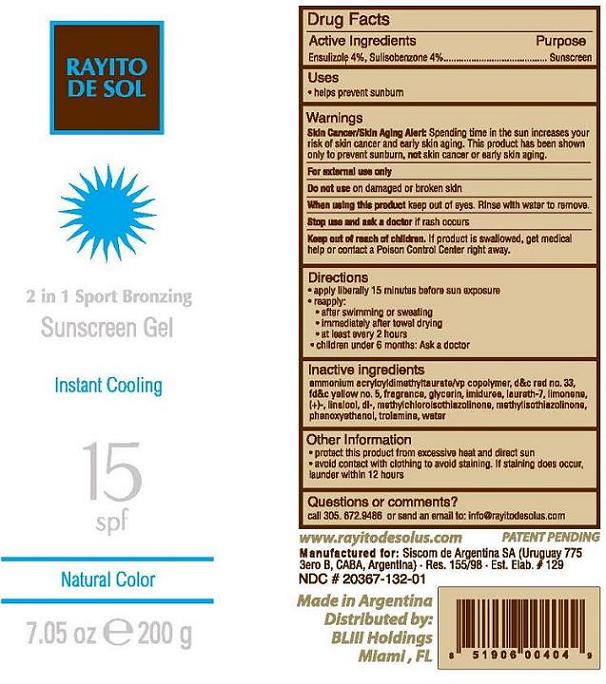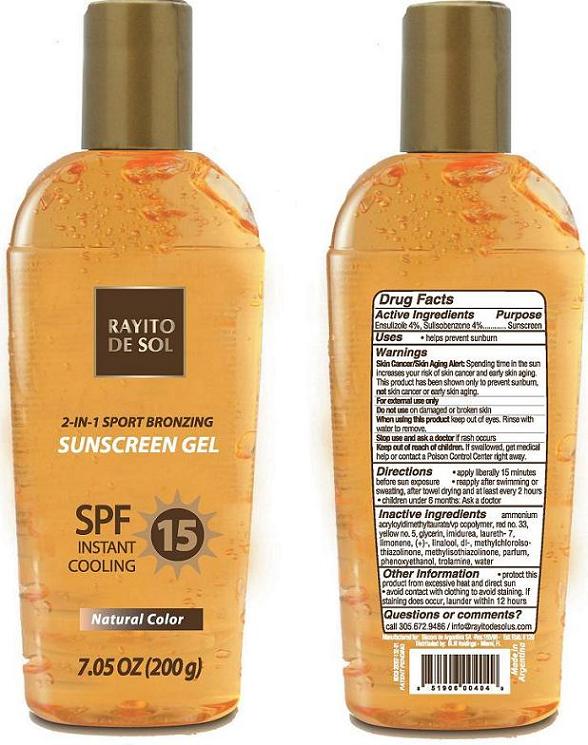 DRUG LABEL: Rayito de Sol
                
                
                
                
NDC: 20367-132 | Form: GEL
Manufacturer: Siscom de Argentina S.A.
Category: otc | Type: HUMAN OTC DRUG LABEL
Date: 20121224

ACTIVE INGREDIENTS: ENSULIZOLE 4 g/200 g; SULISOBENZONE 4 g/200 g
INACTIVE INGREDIENTS: Water; AMMONIUM ACRYLOYLDIMETHYLTAURATE/VP COPOLYMER; GLYCERIN; TROLAMINE; LAURETH-7; IMIDUREA; PHENOXYETHANOL; FD&C YELLOW NO. 5; D&C RED NO. 33; LINALOOL, DL-; LIMONENE, (+/-)-; METHYLCHLOROISOTHIAZOLINONE; METHYLISOTHIAZOLINONE

Rayito de Sol® 2-in-1 Sport Bronzing Susncreen Gel SPF 15 - Natural Color

Active Ingredients

Ensulizole 4%,
Sulisobenzone 4%

Purpose

Sunscreen

Uses

• helps prevent sunburn

Warnings

Skin Cancer/Skin Aging Alert: Spending time in the sun increases your risk of skin cancer and early skin aging.
This product has been shown only to prevent sunburn, not skin cancer or early skin aging.
For external use only

Do not use on damaged or broken skin

When using this product

keep out of eyes. Rinse with water to remove.

Stop use and ask a doctor

if rash occurs

Keep out of the reach of children

If product is swallowed, get medical help or contact a Poison Control Center right away.

Directions

• apply liberally 15 minutes before sun exposure
• reapply:
• after swimming or sweating
• immediately after towel drying
• at least every 2 hours
• children under 6 months: Ask a doctor

Inactive Ingredients

ammonium acryloyldimethyltaurate/vp copolymer, D and C red no. 33, FD and C yellow no. 5, glycerin, imidurea, laureth-7, limonene, (+)-, linalool, dl-, methylchloroisothiazolinone, methylisothiazolinone, parfum, phenoxyethanol, trolamine, water

Other Information

- protect this product from excessive heat and direct sun
- avoid contact with clothing to avoid staining. If staining does occur, launder within 12 hours

Questions or Comments?

call 305.672.9486 or send an email to: info@rayitodesolus.com

Principal Display Panel

RAYITO DE SOL

2-in-1 SPORT BRONZING

SUNSCREEN GEL

INSTANT COOLING

SPF15

Natural Color